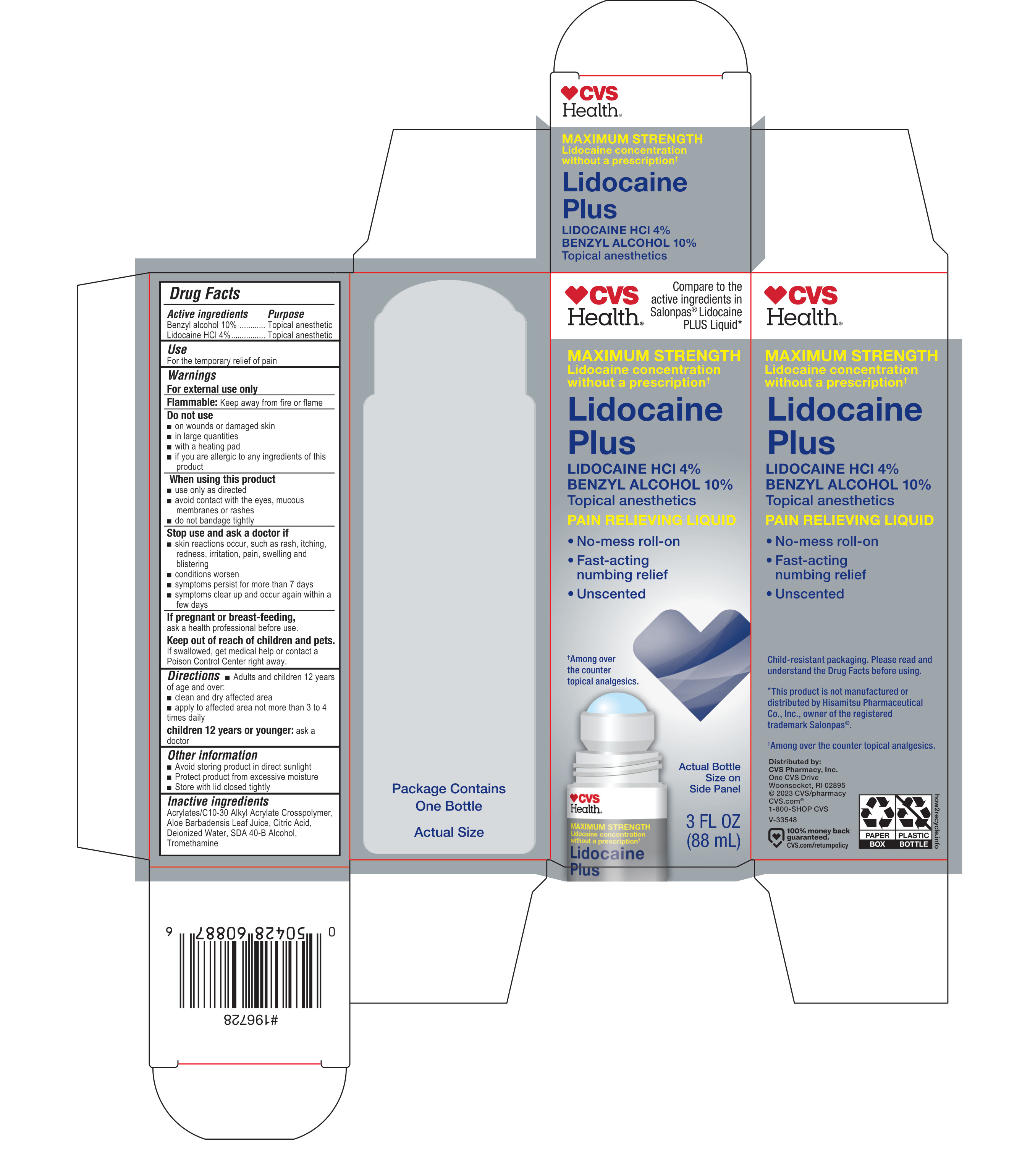 DRUG LABEL: Lidocaine Plus Pain Relieving
NDC: 51316-175 | Form: LIQUID
Manufacturer: CVS Pharmacy
Category: otc | Type: HUMAN OTC DRUG LABEL
Date: 20260122

ACTIVE INGREDIENTS: BENZYL ALCOHOL 100 mg/1 mL; LIDOCAINE HYDROCHLORIDE 40 mg/1 mL
INACTIVE INGREDIENTS: ALOE BARBADENSIS LEAF JUICE; ACRYLATES/C10-30 ALKYL ACRYLATE CROSSPOLYMER (60000 MPA.S); CITRIC ACID; TROMETHAMINE; WATER; ALCOHOL

Lidocaine Plus

Active ingredients

Benzyl alcohol 10%

Lidocaine HCl 4%

Purpose

Topical anesthetic

Topical anesthetic

Use

For the temporary relief of pain

Warnings

For external use only.

Flammable: Keep away from fire or flame

Do not use

- on wounds or damaged skin
- in largge quantities
- with a heating pad
- if you are allergic to any ingredients of this product

When using this product

- use only as directed
- avoid contact with the eyes, mucous membranes or rashes
- do not bandage tightly

Stop use and ask a doctor if

- skin reactions occur, such as rash, itching, redness, irritatin, pain, swelling and blistering
- conditions worsens
- symptoms persist for more than 7 days
- symptoms clear up and occur again within a few days

If pregnant or breast-feeding,

ask a health professional before use.

Keep ot of reach of children and pets.

If swallowed, get medical help or contactg a Poison Control Center right away.

Directions

Adults and children 12 years of age and over:

- clean and dry affected area
- apply to affected area not more than 3 to 4 times daily

Children 12 years or younger: ask a doctor

Other information

- Avoid storing product in direct sunlight
- Protect product from excessive moisture
- Store with lid closed tightly

Inactive ingredients

Acrylates/C10-30 Alkyl Acrylate Crosspolymer, Aloe Barbadensis Leaf Juice, Citric Acid, Deionized Water, SDA 40-B Alcohol, Tromethamine

Principal Display Panel - 88 mL Carton Label

CVS

Health®

Compare to the active ingredients in Salonpas® Lidocaine PLUS Liquid*

MAXIMUM STRENGTH

Lidociane concentration without a prescription†

Lidocaine Plus

Lidocaine HCl 4%

Benzyl Alcohol 10%

Topical anesthetics

Pain Relieving Liquid

- No-mess roll-on
- Fast-acting numbing relief
- Unscented

†Among over the counter topical analgesics

Actual Bottle Size on Side Panel

3 FL OZ (88 mL)